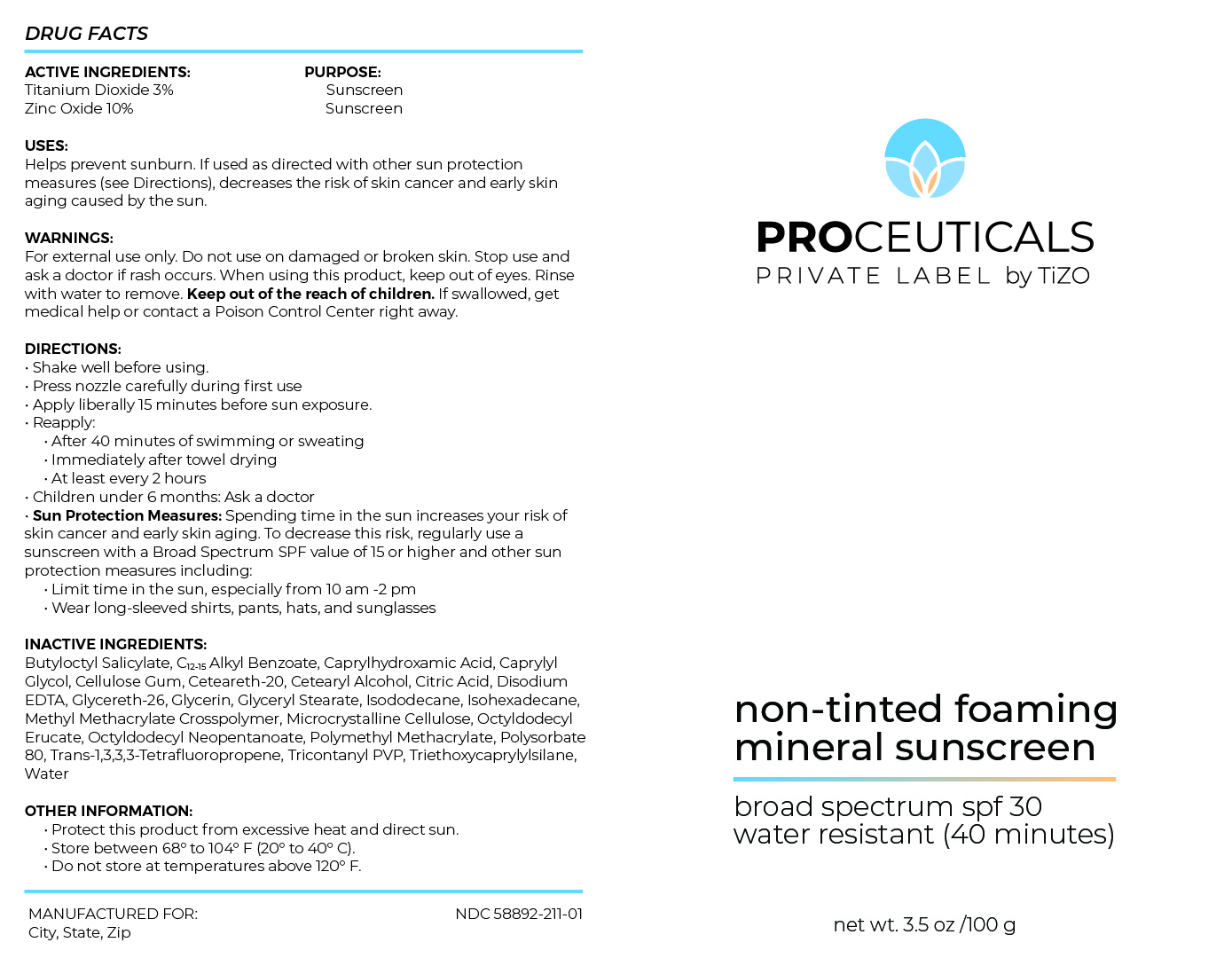 DRUG LABEL: Proceuticals Private Label by TiZO non-tinted foaming mineral sunscreen
NDC: 58892-211 | Form: AEROSOL, FOAM
Manufacturer: Fallien Cosmeceuticals, Ltd
Category: otc | Type: HUMAN OTC DRUG LABEL
Date: 20240809

ACTIVE INGREDIENTS: TITANIUM DIOXIDE 30 mg/1 g; ZINC OXIDE 100 mg/1 g
INACTIVE INGREDIENTS: CETOSTEARYL ALCOHOL; GLYCERETH-26; TRIETHOXYCAPRYLYLSILANE; POLYOXYL 20 CETOSTEARYL ETHER; POLY(METHYL METHACRYLATE; 450000 MW); GLYCERYL MONOSTEARATE; EDETATE DISODIUM ANHYDROUS; ISODODECANE; OCTYLDODECYL NEOPENTANOATE; CITRIC ACID MONOHYDRATE; OCTYLDODECYL ERUCATE; 1,3,3,3-TETRAFLUOROPROPENE, (1E)-; POLYSORBATE 80; METHYL METHACRYLATE/GLYCOL DIMETHACRYLATE CROSSPOLYMER; MICROCRYSTALLINE CELLULOSE; CARBOXYMETHYLCELLULOSE SODIUM, UNSPECIFIED; BUTYLOCTYL SALICYLATE; TRIACONTANYL PVP (WP-660); CAPRYLYL GLYCOL; ALKYL (C12-15) BENZOATE; POLYHYDROXYSTEARIC ACID (2300 MW); WATER; CAPRYLHYDROXAMIC ACID; GLYCERIN

ACTIVE INGREDIENTS:

Titanium Dioxide 3%

Zinc Oxide 10%

PURPOSE:Sunscreen

USES: Helps prevent sunburn. If used as directed with other sun protection
measures (see Directions), decreases the risk of skin cancer and early aging
caused by the sun.

DIRECTIONS:
• Shake well before using.
• Press nozzle carefully during first use
• Apply liberally 15 minutes before sun exposure.
• Reapply:
• After 40 minutes of swimming or sweating
• Immediately after towel drying
• At least every 2 hours
• Children under 6 months: Ask a doctor
• Sun Protection Measures: Spending time in the sun increases your risk of
skin cancer and early skin aging. To decrease this risk, regularly use a
sunscreen with a Broad Spectrum SPF value of 15 or higher and other sun
protection measures including:
• Limit time in the sun, especially from 10 am -2 pm
• Wear long-sleeved shirts, pants, hats, and sunglasses

INACTIVE INGREDIENT

INACTIVE INGREDIENTS:Butyloctyl Salicylate, C12-15 Alkyl Benzoate, Caprylhydroxamic Acid, Caprylyl
Glycol, Cellulose Gum, Ceteareth-20, Cetearyl Alcohol, Citric Acid, Disodium
EDTA, Glycereth-26, Glycerin, Glyceryl Stearate, Isododecane, Isohexadecane,
Methyl Methacrylate Crosspolymer, Microcrystalline Cellulose, Octyldodecyl
Erucate, Octyldodecyl Neopentanoate, Polymethyl Methacrylate, Polysorbate
80, Trans-1,3,3,3-Tetrafluoropropene, Tricontanyl PVP, Triethoxycaprylylsilane,
Water

OTHER INFORMATION:
• Protect this product from excessive heat and direct sun.
• Store between 68° to 104° F (20° to 40° C).
• Do not store at temperatures above 120° F.

WARNINGS:
For external use only. Do not use on damaged or broken skin. Stop use and
ask a doctor if rash occurs. When using this product, keep out of eyes. Rinse
with water to remove. Keep out of the reach of children. If swallowed, get
medical help or contact a Poison Control Center right away.

Keep out of the reach of children.

DOSAGE AND ADMINISTRATION

Helps prevent sunburn. If used as directed with other sun protection
measures (see Directions), decreases the risk of skin cancer and early skin
aging caused by the sun.

Apply liberally 15 minutes befor sun exposure.

Principal Display Panel – 100g Can Label

PROCEUTICALS

PRIVATE LABEL by TiZO

non-tinted foaming

mineral sunscreen

broad spectrum spf 30

water resistant (40 minutes)

net wt. 3.5 oz/ 100 g

Graphic-Untitled